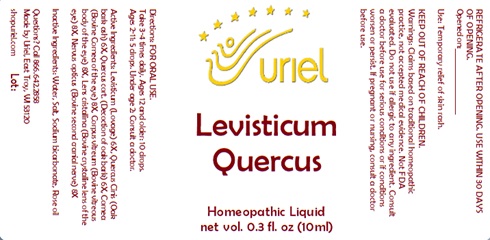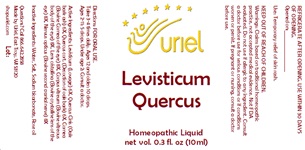 DRUG LABEL: Levisticum Quercus
NDC: 48951-6077 | Form: LIQUID
Manufacturer: Uriel Pharmacy Inc.
Category: homeopathic | Type: HUMAN OTC DRUG LABEL
Date: 20231128

ACTIVE INGREDIENTS: BOS TAURUS PARASYMPATHETIC NERVE 8 [hp_X]/1 mL; QUERCUS ROBUR WHOLE 6 [hp_X]/1 mL; LEVISTICUM OFFICINALE ROOT 6 [hp_X]/1 mL; BOS TAURUS NERVE 8 [hp_X]/1 mL; BOS TAURUS EYE 8 [hp_X]/1 mL; QUERCUS ALBA BARK 6 [hp_X]/1 mL
INACTIVE INGREDIENTS: WATER; SODIUM CHLORIDE; BORIC ACID; SODIUM BICARBONATE; ROSE OIL

Levisticum Quercus

INDICATIONS AND USAGE

Directions: FOR ORAL USE.

DOSAGE AND ADMINISTRATION

Take 3-4 times daily. Ages 12 and older: 10 drops. Ages 2-11: 5 drops. Under age 2: Consult a doctor.

ACTIVE INGREDIENT

Active Ingredients: Levisticum (Lovage) 6X, Quercus Cinis (Oak bark ash) 6X, Quercus (cort.) (Decoction of oak bark) 6X, Cornea (Bovine Cornea of the eye) 8X, Corpus vitreum (Bovine vitreous body of the eye) 8X, Lens cristallina (Bovine crystalline lens of the eye) 8X, Nervus opticus (Bovine second cranial nerve) 8X

INACTIVE INGREDIENT

Inactive Ingredients: Water, Salt, Boric acid, Sodium bicarbonate, Rose oil

PURPOSE

Use: Temporary relief of skin rash.

KEEP OUT OF REACH OF CHILDREN.

WARNINGS

Warnings: Claims based on traditional homeopathic practice, not accepted medical evidence. Not FDA evaluated. Do not use if allergic to any ingredient. Consult a doctor before use for serious conditions or if conditions worsen or persist. If pregnant or nursing, consult a doctor before use. Do not use if safety seal is broken or missing.

REFRIGERATE AFTER OPENING. USE WITHIN 30 DAYS OF OPENING.
Opened on:_________________

Questions? Call 866.642.2858
Made by Uriel, East Troy, WI 53120
shopuriel.com